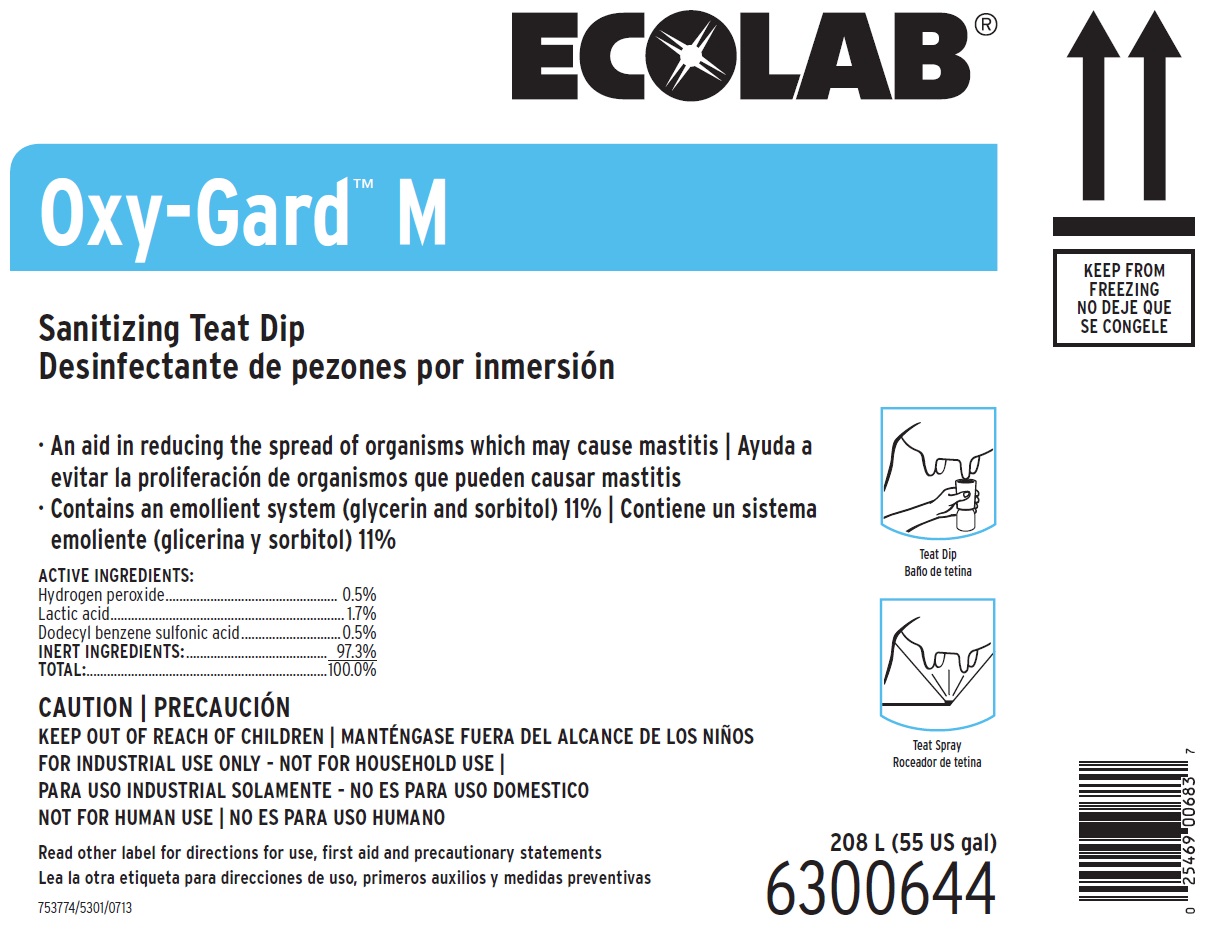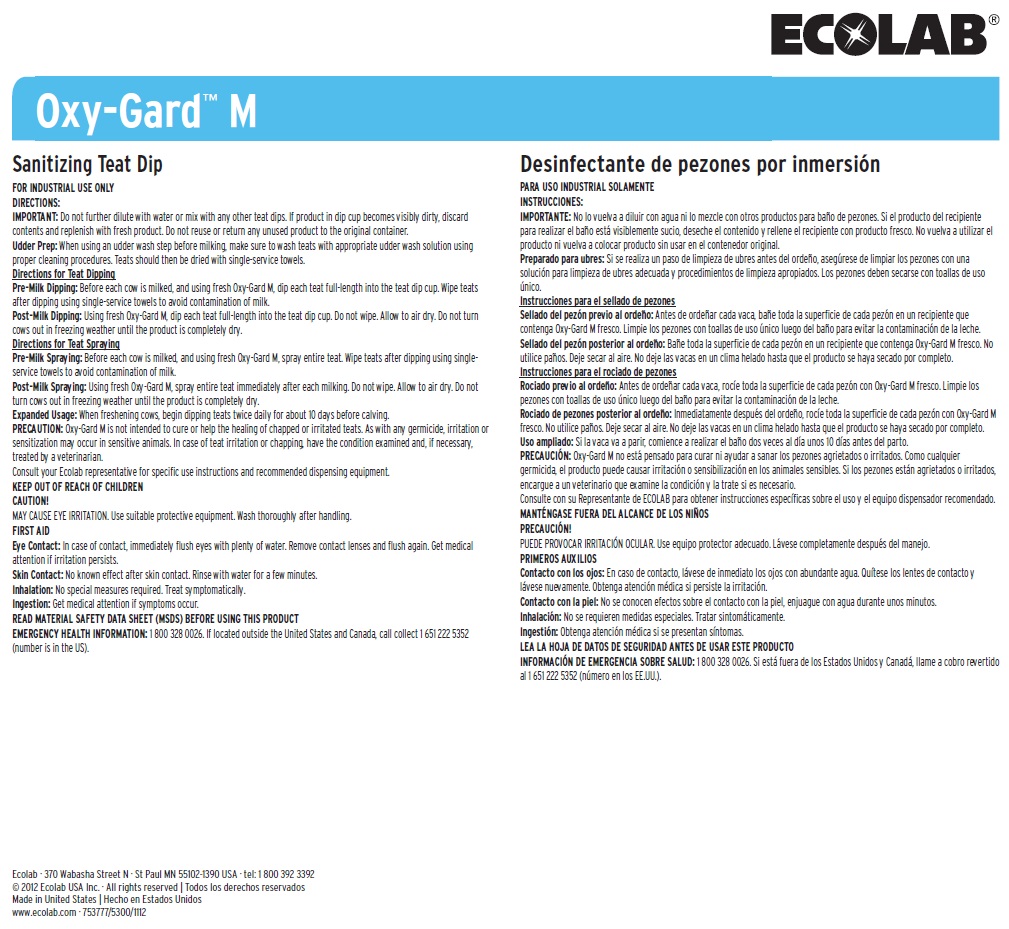 DRUG LABEL: Oxy-Gard M Sanitizing Teat Dip
NDC: 47593-121 | Form: SOLUTION
Manufacturer: Ecolab Inc. 
Category: animal | Type: OTC ANIMAL DRUG LABEL
Date: 20250723

ACTIVE INGREDIENTS: HYDROGEN PEROXIDE 5 mg/1 mL; DODECYLBENZENESULFONIC ACID 5 mg/1 mL; LACTIC ACID 17 mg/1 mL
INACTIVE INGREDIENTS: SORBITOL; GLYCERIN

KEEP OUT OF REACH OF CHILDREN

CAUTION!

MAY CAUSE EYE IRRITATION. Use suitable protective equipment. Wash thoroughly after handling.

FOR INDUSTRIAL USE ONLY - NOT FOR HOUSEHOLD USE

NOT FOR HUMAN USE

Read other label for directions for use, first aid and precautionary statements

DIRECTIONS:

IMPORTANT: Do not further dilute with water or mix with any other teat dips. If product in dip cup becomes visibly dirty, discard contents and replenish with fresh product. Do not reuse or return any unused product to the original container.

Udder Prep: When using an udder wash step before milking, make sure to wash teats with appropriate udder wash solution using proper cleaning procedures. Teats should then be dried with single-service towels.

Directions for Teat Dipping

Pre-Milk Dipping: Before each cow is milked, and using fresh Oxy-Gard M, dip each teat full-length into the teat dip cup. Wipe teats after dipping using single-service towels to avoid contamination of milk.

Post-Milk Dipping: Using fresh Oxy-Gard M, dip each teat full-length into the teat dip cup. Do not wipe. Allow to air dry. Do not turn cows out in freezing weather until the product is completely dry.

Directions for Teat Spraying

Pre-Milk Spraying: Before each cow is milked, and using fresh Oxy-Gard M, spray entire teat. Wipe teats after dipping using single-service towels to avoid contamination of milk.

Post-Milk Spraying: Using fresh Oxy-Gard M, spray entire teat immediately after each milking. Do not wipe. Allow to air dry. Do not turn cows out in freezing weather until the product is completely dry.

Expanded Usage: When freshening cows, begin dipping teats twice daily for about 10 days before calving.

PRECAUTION: Oxy-Gard M is not intended to cure or help the healing of chapped or irritated teats. As with any germicide, irritation or sensitization may occur in sensitive animals. In case of teat irritation or chapping, have the condition examined and, if necessary, treated by a veterinarian.

Consult your Ecolab representative for specific use instructions and recommended dispensing equipment.

OTHER SAFETY INFORMATION

FIRST AID

Eye Contact: In case of contact, immediately flush eyes with plenty of water. Remove contact lenses and flush again. Get medical attention if irritation persists.

Skin Contact: No known effect after skin contact. Rinse with water for a few minutes.

Inhalation: No special measures required. Treat symptomatically.

Ingestion: Get medical attention if symptoms occur.

READ MATERIAL SAFETY DATA SHEET (MSDS) BEFORE USING THIS PRODUCT

EMERGENCY HEALTH INFORMATION: 1 800 328 0026. If located outside the United States and Canada, call collect 1 651 222 5352 (number is in the US).

Principal display panel and representative label

ECOLAB

Oxy-Gard™ M

Sanitizing Teat Dip

An aid in reducing the spread of organisms which may cause mastitis

Contains an emollient system (glycerin and sorbitol) 11%

ACTIVE INGREDIENTS:

Hydrogen peroxide................................................... 0.5%

Lactic acid..................................................................... 1.7%

Dodecyl benzene sulfonic acid..............................0.5%

INERT INGREDIENTS:.......................................... 97.3%

TOTAL:......................................................................100.0%

208 L (55 US gal)

6300644

753774/5301/0713

Ecolab · 370 Wabasha Street N · St Paul MN 55102-1390 USA · tel: 1 800 392 3392

© 2012 Ecolab USA Inc. · All rights reserved

Made in United States

www.ecolab.com · 753777/5300/1112